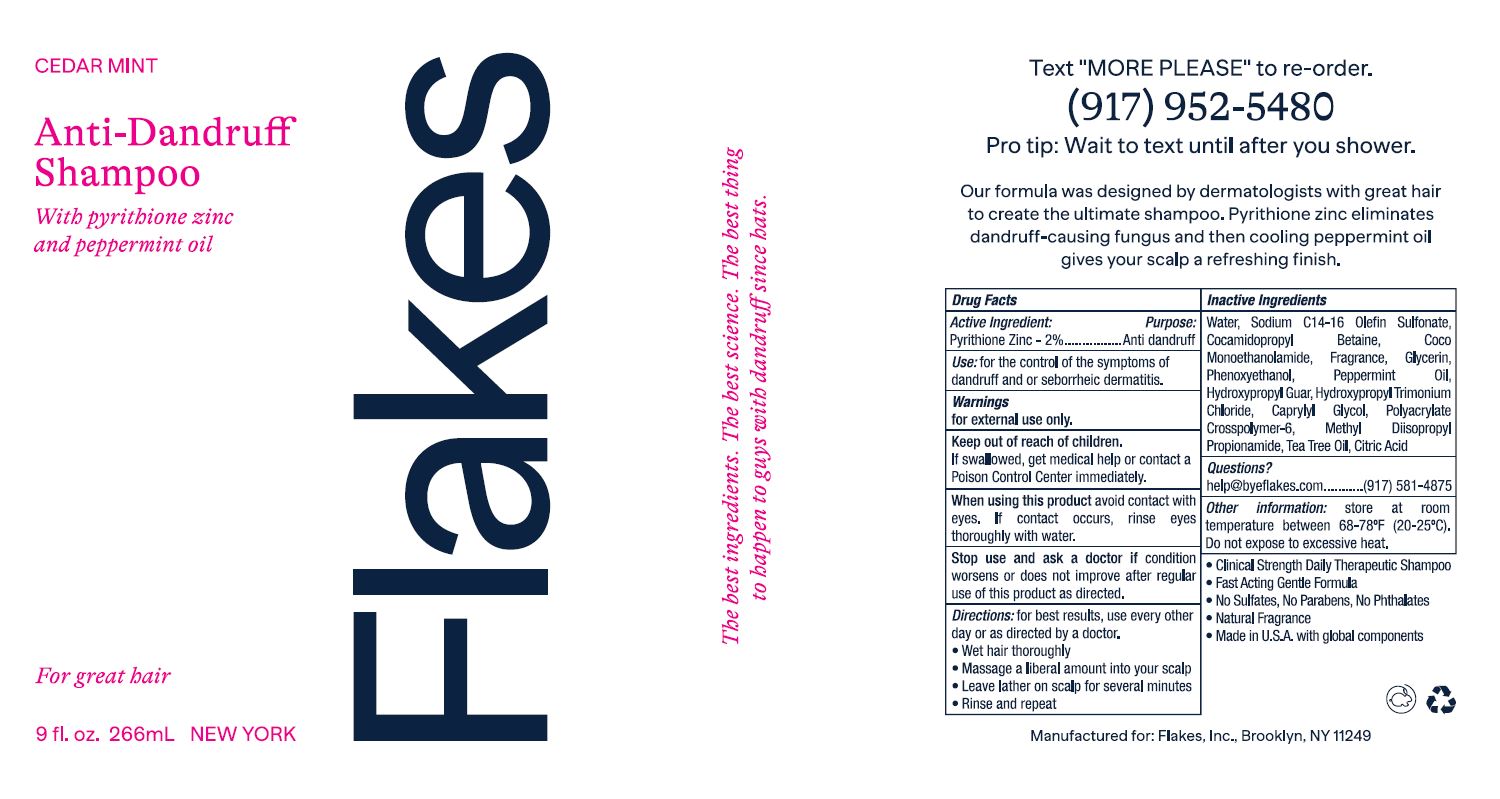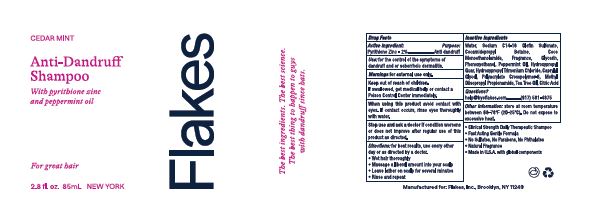 DRUG LABEL: Flakes Cedar Mint Anti Dandruff
NDC: 52261-1400 | Form: LOTION/SHAMPOO
Manufacturer: Cosco International, Inc.
Category: otc | Type: HUMAN OTC DRUG LABEL
Date: 20240521

ACTIVE INGREDIENTS: PYRITHIONE ZINC 0.02 kg/1 kg
INACTIVE INGREDIENTS: WATER; GUARAPROLOSE (1300 MPA.S AT 1%); GUAR HYDROXYPROPYLTRIMONIUM CHLORIDE (1.7 SUBSTITUENTS PER SACCHARIDE); GLYCERIN; AMMONIUM ACRYLOYLDIMETHYLTAURATE, DIMETHYLACRYLAMIDE, LAURYL METHACRYLATE AND LAURETH-4 METHACRYLATE COPOLYMER, TRIMETHYLOLPROPANE TRIACRYLATE CROSSLINKED (45000 MPA.S); COCAMIDOPROPYL BETAINE; COCO MONOETHANOLAMIDE; SODIUM C14-16 OLEFIN SULFONATE; METHYL DIISOPROPYL PROPIONAMIDE; PEPPERMINT OIL; TEA TREE OIL; CITRIC ACID MONOHYDRATE; PHENOXYETHANOL; CAPRYLYL GLYCOL

Flakes Cedar Mint Anti Dandruff Shampoo

DRUG FACTS

Active Ingredients: Purpose:

Pyrithione Zinc 2%..................Anti dandruff

PURPOSE

Use: For the control of the symptoms of dandruff and or seborrheic dermatitis

Warnings

for external use only

Keep out of reach of children.

If swallowed, get medical help or contact a Poison Control Center immediately.

When using this product avoid contact with eyes. If contact occurs, rinse eyes thoroughly with water.

Stop use and ask a doctor if condition worsens or does not improve after regular use of this product as directed.

DOSAGE AND ADMINISTRATION

Directions: for best results, use at least twice a week or as directed by a doctor.
• Wet hair thoroughly
• Massage a liberal amount into your scalp
• Leave lather on scalp for several minutes
• Rinse and repeat.

Inactive Ingredients:
WATER, SODIUM C14-16 OLEFIN SULFONATE, COCAMIDOPROPYL BETAINE, COCO MONOETHANOLAMIDE, FRAGRANCE, GLYCERIN, PHENOXYETHANOL, PEPPERMINT OIL, HYDROXYPROPYL GUAR, HYDROXYPROPYL TRIMONIUM CHLORIDE, CAPRYLYL GLYCOL, POLYACRYLATE CROSSPOLYMER-6, METHYL DIISOPROPYL PROPIONAMIDE, TEA TREE OIL, CITRIC ACID

Questions?

help@byeflakes.com

Other Information
Store at room temperature between 68-77°F (20-25°C).
Do not expose to excessive heat